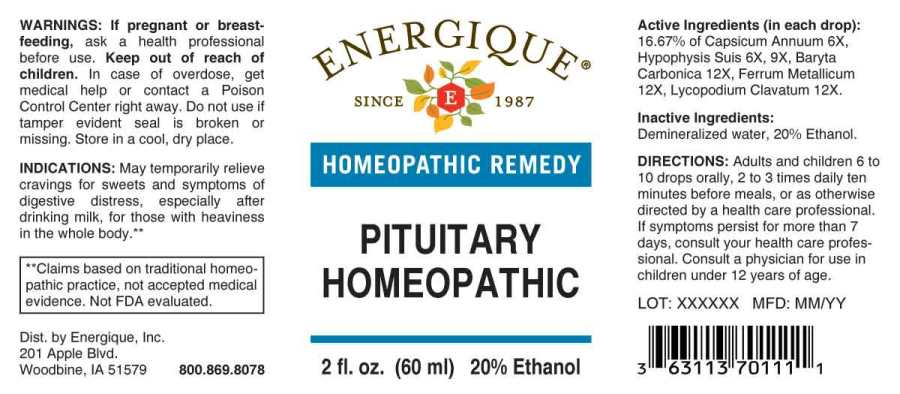 DRUG LABEL: Pituitary Homeopathic
NDC: 44911-0406 | Form: LIQUID
Manufacturer: Energique, Inc.
Category: homeopathic | Type: HUMAN OTC DRUG LABEL
Date: 20241029

ACTIVE INGREDIENTS: CAPSICUM 6 [hp_X]/1 mL; SUS SCROFA PITUITARY GLAND 6 [hp_X]/1 mL; BARIUM CARBONATE 12 [hp_X]/1 mL; IRON 12 [hp_X]/1 mL; LYCOPODIUM CLAVATUM SPORE 12 [hp_X]/1 mL
INACTIVE INGREDIENTS: WATER; ALCOHOL

DRUG FACTS:

ACTIVE INGREDIENTS:

Capsicum Annuum 6X, Hypophysis Suis 6X, 9X, Baryta Carbonica 12X, Ferrum Metallicum 12X, Lycopodium Clavatum 12X.

INDICATIONS:

May temporarily relieve cravings for sweets and symptoms of digestive distress, especially after drinking milk, for those with heaviness in the whole body.**

**Claims based on traditional homeopathic practice, not accepted medical evidence. Not FDA evaluated.

WARNINGS:

If pregnant or breastfeeding, ask a health professional before use.

Keep out of reach of children. In case of overdose, get medical help or contact a Poison Control Center right away.

Do not use if tamper evident seal is broken or missing.

Store in a cool, dry place.

Keep out of reach of children. In case of overdose, get medical help or contact a Poison Control Center right away.

DIRECTIONS:

Adults and children 5 to 10 drops orally, 1 time daily or as otherwise directed by a health care professional. If symptoms persist, consult your health care professional. Consult a physician for use in children under 12 years of age.

INDICATIONS:

May temporarily relieve cravings for sweets and symptoms of digestive distress, especially after drinking milk, for those with heaviness in the whole body.**

**Claims based on traditional homeopathic practice, not accepted medical evidence. Not FDA evaluated.

INACTIVE INGREDIENTS:

Demineralized Water, 20% Ethanol

QUESTIONS:

Dist. by Energique, Inc.
201 Apple Blvd.
Woodbine, IA 51579 800.868.8078

PACKAGE LABEL DISPLAY:

ENERGIQUE
SINCE 1987
PITUITARY
HOMEOPATHIC
2 fl. oz. (60 ml)